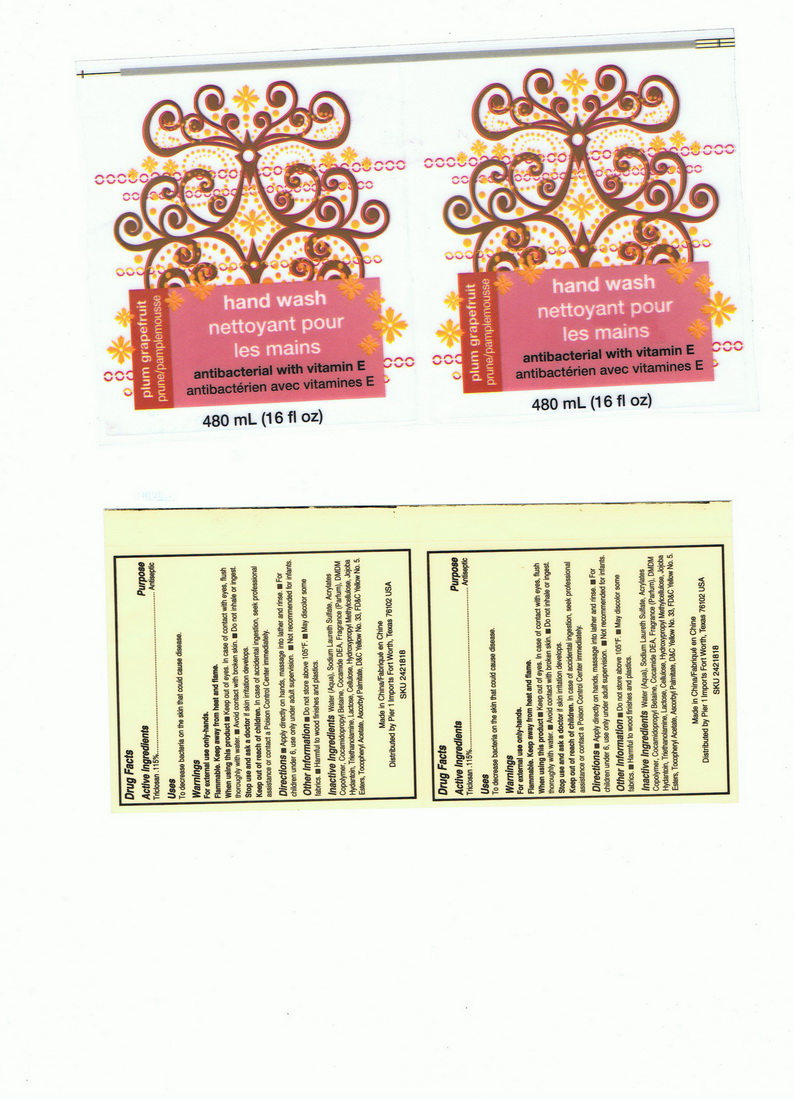 DRUG LABEL: Hand Wash Nettoyant Pour Les Mains Plum Grapefruit
NDC: 49981-004 | Form: LIQUID
Manufacturer: Xiamen Anna Global Co., Ltd
Category: otc | Type: HUMAN OTC DRUG LABEL
Date: 20091116

ACTIVE INGREDIENTS: TRICLOSAN 0.115 g/100 g
INACTIVE INGREDIENTS: WATER 79.854 g/100 g; SODIUM LAURETH SULFATE 9.5 g/100 g; COCAMIDOPROPYL BETAINE 1.5 g/100 g; TROLAMINE 0.775 g/100 g; 1,3-DIMETHYLOL-5,5-DIMETHYL-HYDANTOIN 0.3 g/100 g; ANHYDROUS LACTOSE 0.005 g/100 g; CELLULOSE, MICROCRYSTALLINE 0.005 g/100 g; HYPROMELLOSE 0.01 g/100 g; .ALPHA.-TOCOPHEROL ACETATE, DL- 0.01 g/100 g; ASCORBYL PALMITATE 0.01 g/100 g; D&C RED NO. 33 0.006 g/100 g; FD&C YELLOW NO. 5 0.00001 g/100 g

Drug Fact

Active Ingredient

Active Ingredient Purpose

Triclosan .115% Antiseptic

Uses

To decrease bacteria on the skin that could cause diseases

Warnings

For external use only-hands

Flammable. Keep away from heat and flame.

When use this product Keep out of eyes. In case of contact with eyes,flush thoroughly with water. Avoid contact with broken skin. Do not inhale or ingest.
Stop use and ask a doctor if skin irritation develops.
Keep out of reach of children. In case of accidental ingestion, seek professional assistance or contact a Poison Control Center immediately.

Directions

Apply direct to hands, message into lather and rinse. For children under 6, use only under adult supervision. Not recommended for infants.

Other Information

Do not store above 105F May discolor some fabrics. Harmful to wood finishes and plastics.

Inactive Ingredients

Water (Aqua), Sodium laureth Sulfate, Acrylates Copolymer, Cocamidopropyl Betain, Cocamide DEA, Fragrance, DMDMhydantoin, Triethanolamine, Lactose, Cellulose, Hydroxypropyl Methylcellulose, Jojoba Esters, Tocopheryl Acetate, Ascorbyl Palmitate, D and C Red No. 33, FD and C Yellow No. 5.

Label

this is label